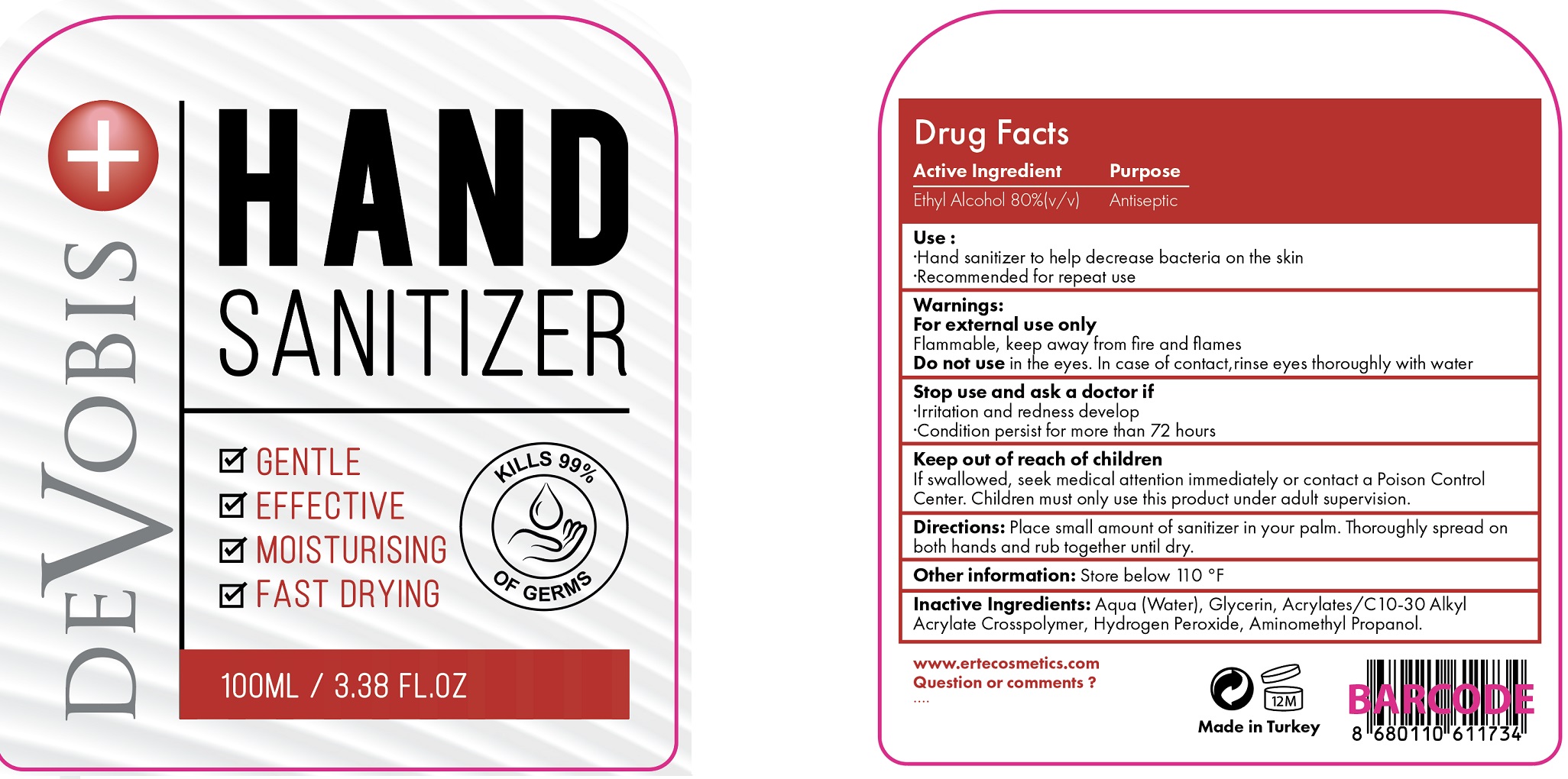 DRUG LABEL: Devobis Hand Sanitizer
NDC: 90030-001 | Form: GEL
Manufacturer: ERTE KOZMETIK SANAYI VE TICARET ANONIM SIRKETI
Category: otc | Type: HUMAN OTC DRUG LABEL
Date: 20200816

ACTIVE INGREDIENTS: ALCOHOL 0.8 mL/1 mL
INACTIVE INGREDIENTS: WATER; GLYCERIN; HYDROGEN PEROXIDE; AMINOMETHYLPROPANOL

Devobis Hand Sanitizer

Active Ingredient

Ethyl Alcohol 80%(v/v)

Purpose

Antiseptic

Use:

- Hand sanitizer to help decrease bacteria on the skin
- Recommended for repeat use

Warnings:

For external use only
Flammable, keep away from fire and flames

Do not use

in the eyes, In case of contact, rinse eyes thoroughly with water

Stop use and ask a doctor if

- Irritation and redness develop
- Condition persist for more than 72 hours

Keep out of reach of children

If swallowed, seek medical attention immediately or contact a Poison Contrl Center. Children must only use this product under adult supervision.

Directions:

Place small amount of sanitizer in your palm. Thoroughly spread on both hands and rub together until dry.

Other information:

Store below 110 °F

Inactive Ingredients:

Aqua (Water), Glycerin, Acrylates/C 10-30 Alkyl Acrylate Crosspolymer, Hydrogen Peroxide, Aminomethyl Propanol.